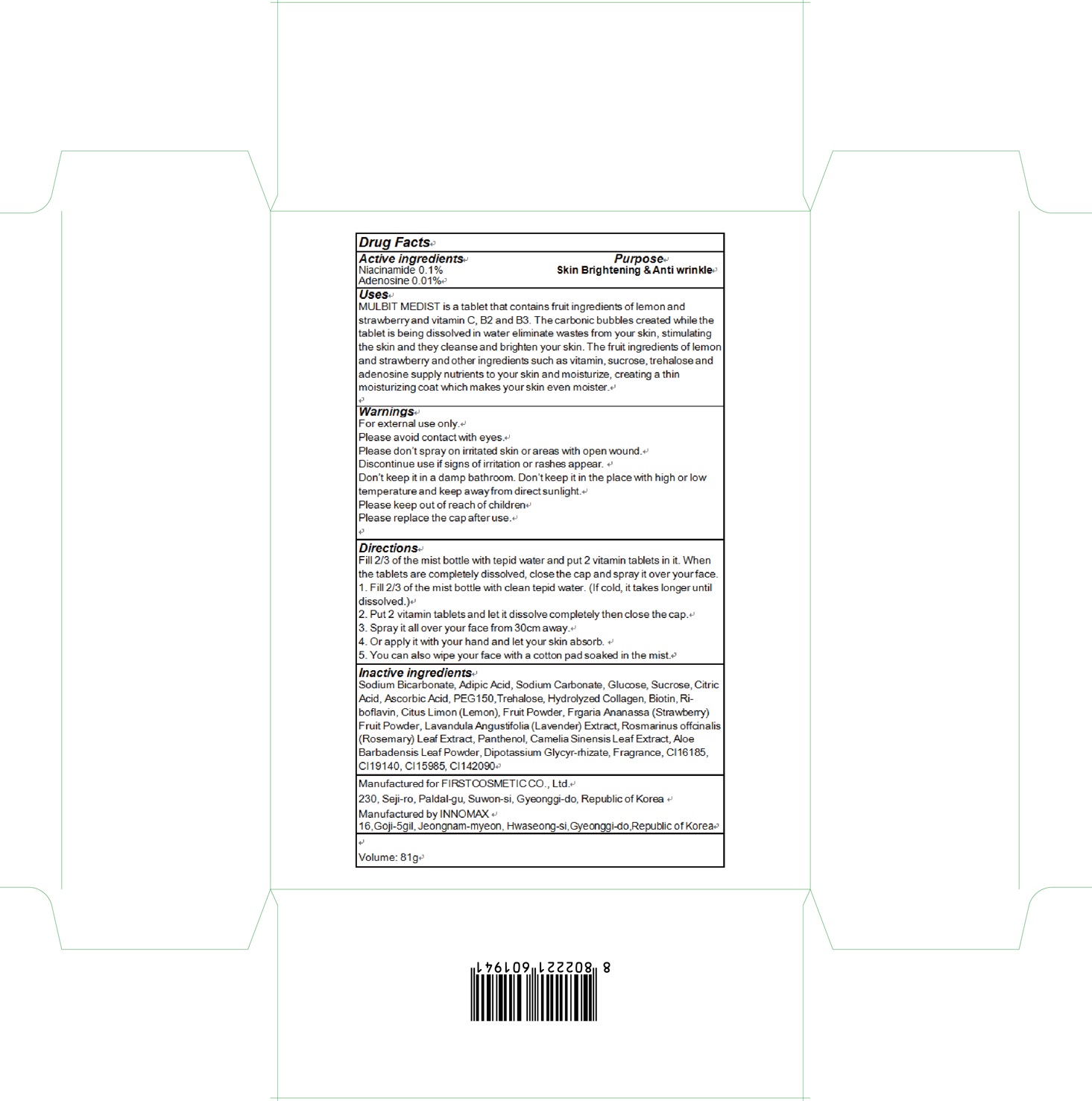 DRUG LABEL: MULBIT
NDC: 71635-090 | Form: LIQUID
Manufacturer: First Cosmetic Co., Ltd
Category: otc | Type: HUMAN OTC DRUG LABEL
Date: 20171026

ACTIVE INGREDIENTS: Niacinamide 0.08 g/81 g; Adenosine 0.008 g/81 g
INACTIVE INGREDIENTS: Sodium Bicarbonate; Adipic Acid

ACTIVE INGREDIENT

Active ingredients: Niacinamide 0.1%, Adenosine 0.01%

INACTIVE INGREDIENT

Inactive ingredients: Sodium Bicarbonate, Adipic Acid, Sodium Carbonate, Glucose, Sucrose, Citric Acid, Ascorbic Acid, PEG150,Trehalose, Hydrolyzed Collagen, Biotin, Ri-boflavin, Citus Limon (Lemon), Fruit Powder, Frgaria Ananassa (Strawberry) Fruit Powder, Lavandula Angustifolia (Lavender) Extract, Rosmarinus offcinalis (Rosemary) Leaf Extract, Panthenol, Camelia Sinensis Leaf Extract, Aloe Barbadensis Leaf Powder, Dipotassium Glycyr-rhizate, Fragrance, CI16185, CI19140, CI15985, CI142090

PURPOSE

Purpose: Skin Brightening & Anti wrinkle

WARNINGS

Warnings: For external use only. Please avoid contact with eyes. Please don’t spray on irritated skin or areas with open wound. Discontinue use if signs of irritation or rashes appear. Don’t keep it in a damp bathroom. Don’t keep it in the place with high or low temperature and keep away from direct sunlight. Please keep out of reach of children Please replace the cap after use.

KEEP OUT OF REACH OF CHILDREN

Uses

Uses: MULBIT MEDIST is a tablet that contains fruit ingredients of lemon and strawberry and vitamin C, B2 and B3. The carbonic bubbles created while the tablet is being dissolved in water eliminate wastes from your skin, stimulating the skin and they cleanse and brighten your skin. The fruit ingredients of lemon and strawberry and other ingredients such as vitamin, sucrose, trehalose and adenosine supply nutrients to your skin and moisturize, creating a thin moisturizing coat which makes your skin even moister.

Directions

Directions: Fill 2/3 of the mist bottle with tepid water and put 2 vitamin tablets in it. When the tablets are completely dissolved, close the cap and spray it over your face. 1. Fill 2/3 of the mist bottle with clean tepid water. (If cold, it takes longer until dissolved.) 2. Put 2 vitamin tablets and let it dissolve completely then close the cap. 3. Spray it all over your face from 30cm away. 4. Or apply it with your hand and let your skin absorb. 5. You can also wipe your face with a cotton pad soaked in the mist.